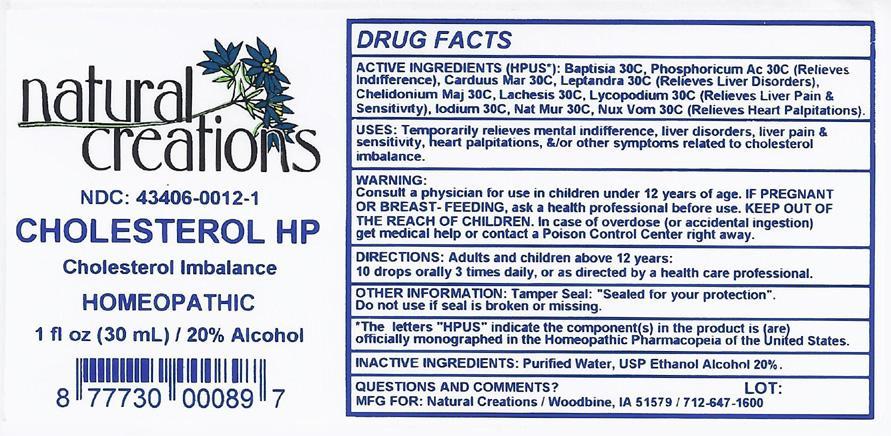 DRUG LABEL: Cholesterol HP
NDC: 43406-0012 | Form: LIQUID
Manufacturer: Natural Creations, Inc.
Category: homeopathic | Type: HUMAN OTC DRUG LABEL
Date: 20121015

ACTIVE INGREDIENTS: BAPTISIA TINCTORIA ROOT 30 [hp_C]/1 mL; SILYBUM MARIANUM SEED 30 [hp_C]/1 mL; CHELIDONIUM MAJUS 30 [hp_C]/1 mL; IODINE 30 [hp_C]/1 mL; LACHESIS MUTA VENOM 30 [hp_C]/1 mL; VERONICASTRUM VIRGINICUM ROOT 30 [hp_C]/1 mL; LYCOPODIUM CLAVATUM SPORE 30 [hp_C]/1 mL; SODIUM CHLORIDE 30 [hp_C]/1 mL; STRYCHNOS NUX-VOMICA SEED 30 [hp_C]/1 mL; PHOSPHORIC ACID 30 [hp_C]/1 mL
INACTIVE INGREDIENTS: WATER; ALCOHOL

Cholesterol HP

ACTIVE INGREDIENT

Active Ingredients (HPUS*): Baptisia Tinctoria 30C, Carduus Marianus 30C, Chelidonium Majus 30C, Iodium 30C, Lachesis Mutus 30C, Leptandra Virginica 30C, Lycopodium Clavatum 30C, Natrum Muriaticum 30C, Nux Vomica 30C, Phosphoricum Acidum 30C

INDICATIONS AND USAGE

USES: Temporarily relieves mental indifference, liver disorders, liver pain & sensitivity, heart palpitations, &/or other symptoms related to cholesterol imbalance.

WARNING:

Consult a physician for use in children under 12 years of age. IF PREGNANT OR BREAST-FEEDING, ask a health care professional before use. KEEP OUT OF THE REACH OF CHILDREN. In case of overdose (or accidental ingestion) get medical help or contact a Poison Control Center right away.

DOSAGE AND ADMINISTRATION

DIRECTIONS: Adults and children above 12 years: 10 drops orally 3 times daily, or as directed by a health care professional.

OTHER INFORMATION: Tamper Seal: "Sealed for your protection."

Do not use if seal is broken or missing

REFERENCES

*The letters "HPUS" indicate the components in the product are officially monographed in the Homeopathic Pharmacopeia of the United States.

INACTIVE INGREDIENTS: Purified Water, USP Ethanol 20%

QUESTIONS AND COMMENTS?

MFG FOR: Natural Creations / Woodbine, IA / 51579 712.647.1600

LOT:

PURPOSE

USES: Temporarily relieves mental indifference, liver disorders, liver pain & sensitivity, heart palpitations, &/or other symptoms related to cholesterol imbalance.

KEEP OUT OF REACH OF CHILDREN

KEEP OUT OF THE REACH OF CHILDREN: in case of overdose (or accidental ingestion) get medical help or contact a Poison Control Center.

PACKAGE LABEL

NDC: 43406-0012-1

CHOLESTEROL HP

Cholesterol Imbalance

HOMEOPATHIC
1 fl oz (30 mL) / 20% Alcohol

UPC: 87730000897